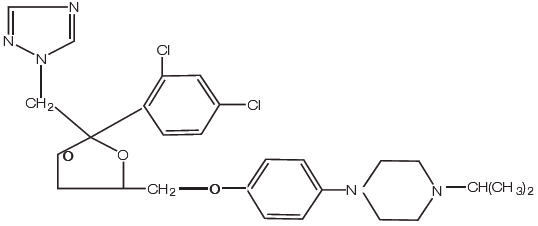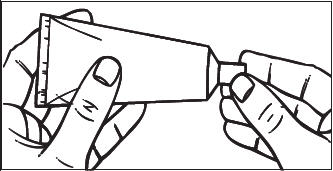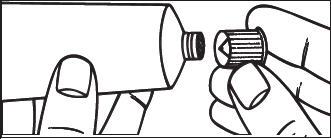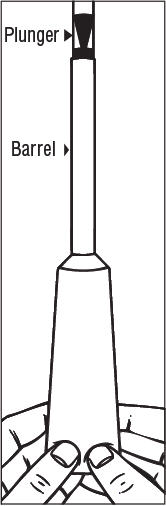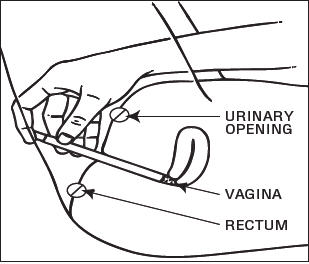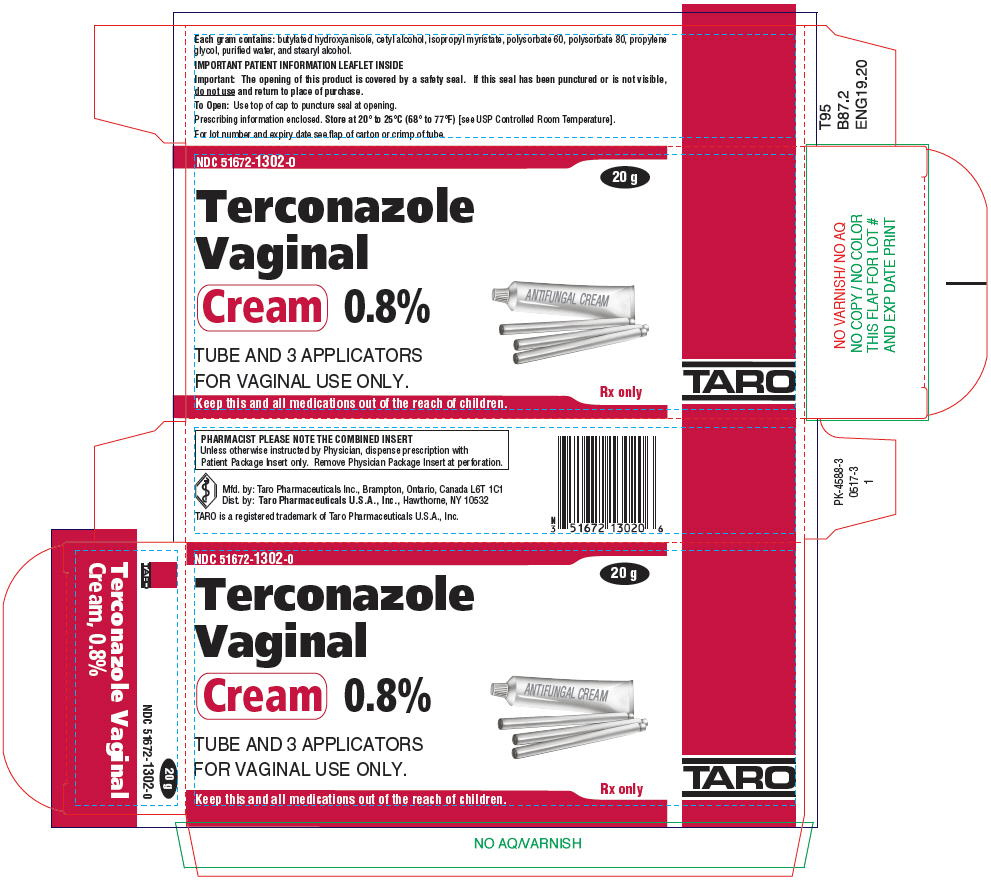 DRUG LABEL: Terconazole
NDC: 51672-1302 | Form: CREAM
Manufacturer: Sun Pharmaceutical Industries, Inc.
Category: prescription | Type: HUMAN PRESCRIPTION DRUG LABEL
Date: 20250707

ACTIVE INGREDIENTS: TERCONAZOLE 8 mg/1 g
INACTIVE INGREDIENTS: BUTYLATED HYDROXYANISOLE; CETYL ALCOHOL; ISOPROPYL MYRISTATE; POLYSORBATE 60; POLYSORBATE 80; PROPYLENE GLYCOL; WATER; STEARYL ALCOHOL

Terconazole
Vaginal Cream 0.8%

Rx Only

DESCRIPTION

Terconazole Vaginal Cream 0.8% is a white to off-white, water washable cream for intravaginal administration containing 0.8% of the antifungal agent terconazole, cis-1-[ p-[[2-(2,4-Dichlorophenyl)-2-(1 H-1,2,4-triazol-1-ylmethyl)-1,3-dioxolan-4-yl]methoxy]phenyl]-4-isopropylpiperazine, compounded in a cream base consisting of butylated hydroxyanisole, cetyl alcohol, isopropyl myristate, polysorbate 60, polysorbate 80, propylene glycol, purified water, and stearyl alcohol.

The structural formula of terconazole is as follows:

TERCONAZOLE
C26H31Cl2N5O3

Terconazole, a triazole derivative, is a white to almost white powder with a molecular weight of 532.47. It is insoluble in water; sparingly soluble in ethanol; and soluble in butanol.

CLINICAL PHARMACOLOGY

Absorption

Following a single intravaginal application of a suppository containing 240 mg^14C-terconazole to healthy women, approximately 70% (range: 64 to 76%) of terconazole remains in the vaginal area during the suppository retention period (16 hours); approximately 10% (range: 5 to 16%) of the administered radioactivity was absorbed systemically over 7 days. Maximum plasma concentrations of terconazole occur 5 to 10 hours after intravaginal application of the cream or suppository. Systemic exposure to terconazole is approximately proportional to the applied dose, whether as the cream or suppository. The rate and extent of absorption of terconazole are similar in patients with vulvovaginal candidiasis (pregnant or non-pregnant) and healthy subjects.

Distribution

Terconazole is highly protein bound (94.9%) in human plasma and the degree of binding is independent of drug concentration over the range of 0.01 to 5 mcg/mL.

Metabolism

Systemically absorbed terconazole is extensively metabolized (>95%).

Elimination

Across various studies in healthy women, after single or multiple intravaginal administration of terconazole as the cream or suppository/ovule, the mean elimination half-life of unchanged terconazole ranged from 6.4 to 8.5 hours. Following a single intravaginal administration of a suppository containing 240 mg^14C-terconazole to hysterectomized or tubal ligated women, approximately 3 to 10% (mean ± SD: 5.7 ± 3%) of the administered radioactivity was eliminated in the urine and 2 to 6% (mean ± SD: 4.2 ± 1.6%) was eliminated in the feces during the 7-day collection period.

Multiple Dosing

There is no significant increase in maximum plasma concentration or overall exposure (AUC) after multiple daily applications of the cream for 7 days or suppositories for 3 days.

Photosensitivity reactions were observed in some normal volunteers following repeated dermal application of terconazole 2% and 0.8% creams under conditions of filtered artificial ultraviolet light.

Photosensitivity reactions have not been observed in U.S. and foreign clinical trials in patients who were treated with terconazole suppositories or vaginal cream (0.4% and 0.8%).

Microbiology

Mechanism of action

Terconazole, an azole antifungal agent, inhibits fungal cytochrome P-450-mediated 14 alpha-lanosterol demethylase enzyme. This enzyme functions to convert lanosterol to ergosterol. The accumulation of 14 alpha-methyl sterols correlates with the subsequent loss of ergosterol in the fungal cell wall and may be responsible for the antifungal activity of terconazole. Mammalian cell demethylation is less sensitive to terconazole inhibition.

Activity in vitro

Terconazole exhibits antifungal activity in vitroagainst Candida albicansand other Candidaspecies. The MIC values of terconazole against most Lactobacillusspp. typically found in the human vagina were ≥128 mcg/mL; therefore these beneficial bacteria are not affected by drug treatment.

INDICATIONS AND USAGE

Terconazole vaginal cream is indicated for the local treatment of vulvovaginal candidiasis (moniliasis). As terconazole vaginal cream is effective only for vulvovaginitis caused by the genus Candida, the diagnosis should be confirmed by KOH smears and/or cultures.

CONTRAINDICATIONS

Patients known to be hypersensitive to terconazole or to any of the components of the cream.

WARNINGS

Anaphylaxis and toxic epidermal necrolysis have been reported during terconazole therapy. Terconazole therapy should be discontinued if anaphylaxis or toxic epidermal necrolysis develops.

PRECAUTIONS

General

For vulvovaginal use only. Terconazole is not for ophthalmic or oral use. Discontinue use and do not retreat with terconazole if sensitization, irritation, fever, chills or flu-like symptoms are reported during use.

Laboratory Tests

If there is lack of response to terconazole, appropriate microbiologic studies (standard KOH smear and/or cultures) should be repeated to confirm the diagnosis and rule out other pathogens.

Drug Interactions

The therapeutic effect of terconazole is not affected by oral contraceptive usage.

The levels of estradiol and progesterone did not differ significantly when 0.8% terconazole vaginal cream was administered to healthy female volunteers established on a low dose oral contraceptive.

Carcinogenesis, Mutagenesis, Impairment of Fertility

Carcinogenesis

Studies to determine the carcinogenic potential of terconazole have not been performed.

Mutagenicity

Terconazole was not mutagenic when tested in vitrofor induction of microbial point mutations (Ames test), or for inducing cellular transformation, or in vivofor chromosome breaks (micronucleus test) or dominant lethal mutations in mouse germ cells.

Impairment of Fertility

No impairment of fertility occurred when female rats were administered terconazole orally up to 40 mg/kg/day for a three month period.

Pregnancy

Teratogenic Effects

Pregnancy Category C

There was no evidence of teratogenicity when terconazole was administered orally up to 40 mg/kg/day (50× the recommended intravaginal human dose of the 0.8% vaginal cream formulation) in rats, or 20 mg/kg/day in rabbits, or subcutaneously up to 20 mg/kg/day in rats.

Dosages at or below 10 mg/kg/day produced no embryotoxicity; however, there was a delay in fetal ossification at 10 mg/kg/day in rats. There was some evidence of embryotoxicity in rabbits and rats at 20 to 40 mg/kg. In rats, this was reflected as a decrease in litter size and number of viable young and reduced fetal weight. There was also delay in ossification and an increased incidence of skeletal variants.

The no-effect dose of 10 mg/kg/day resulted in a mean peak plasma level of terconazole in pregnant rats of 0.176 mcg/mL which exceeds by 30 times the mean peak plasma level (0.006 mcg/mL) seen in normal subjects after intravaginal administration of terconazole 0.8% vaginal cream. This safety assessment does not account for possible exposure of the fetus through direct transfer to terconazole from the irritated vagina by diffusion across amniotic membranes.

Since terconazole is absorbed from the human vagina, it should not be used in the first trimester of pregnancy unless the physician considers it essential to the welfare of the patient.

Terconazole may be used during the second and third trimester if the potential benefit outweighs the possible risks to the fetus.

Nursing Mothers

It is not known whether this drug is excreted in human milk. Animal studies have shown that rat offspring exposed via the milk of treated (40 mg/kg/orally) dams showed decreased survival during the first few post-partum days, but overall pup weight and weight gain were comparable to or greater than controls throughout lactation. Because many drugs are excreted in human milk, and because of the potential for adverse reaction in nursing infants from terconazole, a decision should be made whether to discontinue nursing or to discontinue the drug, taking into account the importance of the drug to the mother.

Pediatric Use

Safety and efficacy in children have not been established.

Geriatric Use

Clinical studies of terconazole did not include sufficient numbers of subjects aged 65 and over to determine whether they respond differently from younger subjects. Other reported clinical experience has not identified differences in responses between the elderly and younger patients.

ADVERSE REACTIONS

Adverse Reactions from Clinical Trials

Because clinical trials are conducted under widely varying conditions, adverse reaction rates observed in the clinical trials of a drug cannot be directly compared to rates in the clinical trials of another drug and may not reflect the rates observed in clinical practice.

During controlled clinical studies conducted in the United States, patients with vulvovaginal candidiasis were treated with terconazole 0.8% vaginal cream for three days. Based on comparative analyses with placebo and a standard agent, the adverse experiences considered most likely related to terconazole 0.8% vaginal cream were headache (21% vs. 16% with placebo) and dysmenorrhea (6% vs. 2% with placebo). Other adverse experiences reported with terconazole 0.8% vaginal cream were abdominal pain (3.4% vs. 1% with placebo) and fever (1% vs. 0.3% with placebo). The adverse drug experience most frequently causing discontinuation of therapy was vulvovaginal itching, 0.7% with the terconazole 0.8% vaginal cream group and 0.3% with the placebo group.

Post-marketing Experience

The following adverse drug reactions have been first identified during post-marketing experience with terconazole:. Because these reactions are reported voluntarily from a population of uncertain size, it is not always possible to reliably estimate their frequency or establish a causal relationship to drug exposure.

General: Asthenia, Influenza-Like Illness consisting of multiple listed reactions including fever and chills, nausea, vomiting, myalgia, arthralgia, malaise

Immune: Hypersensitivity, Anaphylaxis, Face Edema

Nervous: Dizziness

Respiratory: Bronchospasm

Skin: Rash, Toxic Epidermal Necrolysis, Urticaria

OVERDOSAGE

In the rat, the oral LD50values were found to be 1741 and 849 mg/kg for the male and female, respectively. The oral LD50values for the male and female dog were ≅1280 and ≥640 mg/kg, respectively.

In the event of oral ingestion of suppository or cream, supportive and symptomatic measures should be carried out. If the cream is accidentally applied to the eyes, wash with clean water or saline and seek medical attention if symptoms persist.

DOSAGE AND ADMINISTRATION

One full applicator (5 grams) of terconazole vaginal cream (40 mg terconazole) should be administered intravaginally once daily at bedtime for three consecutive days.

Before prescribing another course of therapy, the diagnosis should be reconfirmed by smears and/or cultures and other pathogens commonly associated with vulvovaginitis ruled out. The therapeutic effect of terconazole vaginal cream is not affected by menstruation.

HOW SUPPLIED

Terconazole Vaginal Cream 0.8% is available in 20 gram (NDC 51672-1302-0) tubes with 3 measured-dose applicators.

STORAGE AND HANDLING

Store at 20° to 25°C (68° to 77°F)[see USP Controlled Room Temperature].

Mfd. by: Taro Pharmaceuticals Inc., Brampton, Ontario, Canada L6T 1C1
Dist. by: Taro Pharmaceuticals U.S.A., Inc.,Hawthorne, NY 10532

Revised: October, 2019
PK-4589-6 55

Terconazole Vaginal Cream 0.8%

PATIENT INSTRUCTIONS

FILLING THE APPLICATOR:

1. 1.Remove the cap from the tube.
2. 2.Use the pointed tip on the top of the cap to puncture the seal on the tube.
3. 3.Screw the applicator onto the tube.
4. 4.Squeeze the tube from the bottom and fill the applicator until the plunger stops.
  DO NOT release pressure on the tube until you have separated it from the filled applicator.
5. 5.Unscrew the applicator from the tube.
  After each use, replace the cap and roll up the tube from the bottom.

USING THE APPLICATOR:

1. 1.Lie on your back with your knees drawn up toward your chest.
2. 2.Holding the applicator by the ribbed end of the barrel, insert the filled applicator into the vagina as far as it will comfortably go.
3. 3.Slowly press the plunger of the applicator to release the cream into the vagina.
4. 4.Remove the applicator from the vagina.
5. 5.Apply one applicatorful each night for 3 nights at bedtime, as directed by your doctor.
  Discard the applicator after each use.

NOTE: Store at 20° to 25°C (68° to 77°F)[see USP Controlled Room Temperature]. See end flap of carton or crimp of tube for lot number and expiration date.

A WORD ABOUT YEAST INFECTIONS

Why do yeast infections occur?

Yeast infections are caused by an organism called Candida(KAN di duh). It may be present in small and harmless amounts in the mouth, digestive tract, and vagina. Sometimes the natural balance of the vagina becomes upset. This may lead to rapid growth of Candida,which results in a yeast infection. Symptoms of a yeast infection include itching, burning, redness, and an abnormal discharge. Your doctor can make the diagnosis of a yeast infection by evaluating your symptoms and looking at a sample of the discharge under the microscope.

How can I prevent yeast infections?

Certain factors may increase your chance of developing a yeast infection. These factors don't actually cause the problem, but they may create a situation that allows the yeast to grow rapidly.

- Clothing:Tight jeans, nylon underwear, pantyhose, and wet bathing suits can hold in heat and moisture (two conditions in which yeast organisms thrive). Looser pants or skirts, 100% cotton underwear, and stockings may help avoid this problem.
- Diet:Cutting down on sweets, milk products, and artificial sweeteners may reduce the risk of yeast infections.
- Antibiotics:Antibiotics work by eliminating disease-causing organisms. While they are helpful in curing other problems, antibiotics may lead to an overgrowth of Candidain the vagina.
- Pregnancy:Hormonal changes in the body during pregnancy encourage the growth of yeast. This is a very common time for an infection to occur. Until the baby is born, it may be hard to completely eliminate yeast infections. If you believe you are pregnant, tell your doctor.
- Menstruation:Sometimes monthly changes in hormone levels may lead to yeast infections.
- Diabetes:In addition to heat and moisture, yeast thrives on sugar. Because diabetics often have sugar in their urine, their vaginas are rich in this substance. Careful control of diabetes may help prevent yeast infection.

Controlling these factors can help eliminate yeast infections and may prevent them from coming back.

Some other helpful tips:

1. 1.For best results, be sure to use the medication as prescribed by your doctor, even if you feel better quickly.
2. 2.Avoid sexual intercourse, if your doctor advises you to do so.
3. 3.If your partner has any penile itching, redness, or discomfort, he should consult his physician and mention that you are being treated for a yeast infection.
4. 4.You can use the medication even if you are having your menstrual period. However, you should not use tampons because they may absorb the medication. Instead, use external pads or napkins until you have finished your medication. You may also wish to wear a sanitary napkin if the vaginal medication leaks.
5. 5.Dry the genital area thoroughly after showering, bathing, or swimming. Change out of a wet bathing suit or damp exercise clothes as soon as possible. A dry environment is less likely to encourage the growth of yeast.
6. 6.Wipe from front to rear (away from the vagina) after a bowel movement.
7. 7.Don't douche unless your doctor specifically tells you to do so. Douching may disturb the vaginal balance.
8. 8.Don't scratch if you can help it. Scratching can cause more irritation and spread the infection.
9. 9.Discuss with your physician any medication you are already taking. Certain types of medication can make your vagina more susceptible to infection.
10. 10.Eat nutritious meals to promote your general health.

Mfd. by:
Taro Pharmaceuticals Inc.
Brampton, Ontario, Canada L6T 1C1

Dist. by:
Taro Pharmaceuticals U.S.A., Inc.
Hawthorne, NY 10532

Revised: October, 2019
PK-4589-6 55

PRINCIPAL DISPLAY PANEL - 20 g Tube Carton

NDC 51672-1302-0

20 g

Terconazole
Vaginal
Cream 0.8%

TUBE AND 3 APPLICATORS
FOR VAGINAL USE ONLY.

Rx only

Keep this and all medications out of the reach of children.

TARO